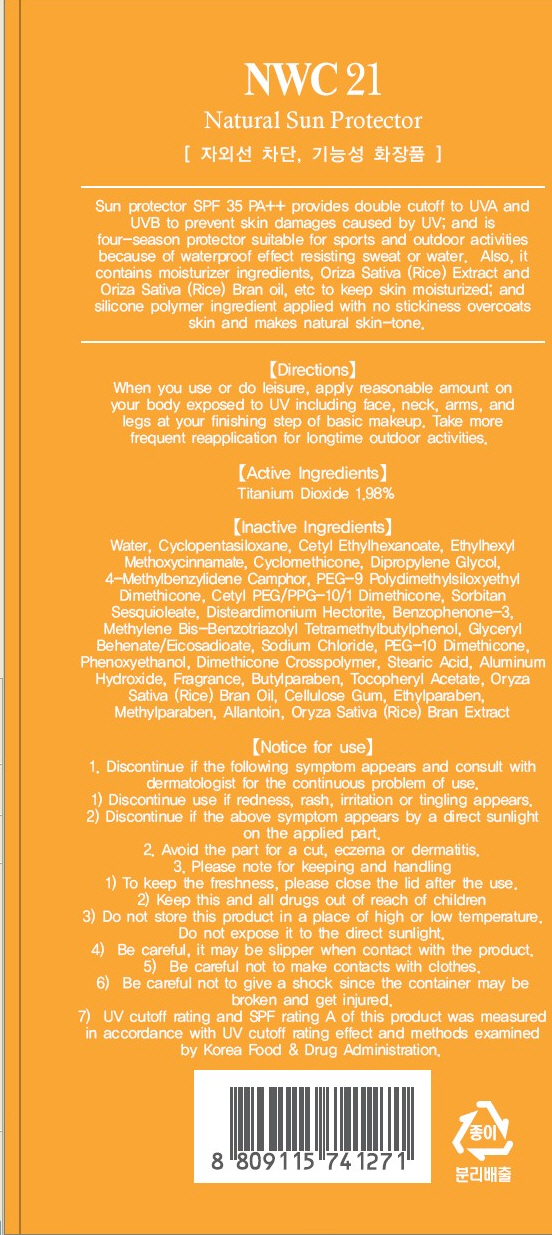 DRUG LABEL: NWC21 NATURAL SUN PROTECTOR
NDC: 45167-030 | Form: CREAM
Manufacturer: CLEANSIA CORPORATION LTD.
Category: otc | Type: HUMAN OTC DRUG LABEL
Date: 20100901

ACTIVE INGREDIENTS: TITANIUM DIOXIDE 1.18 mL/60 mL

Drug Facts

Active Ingredient: TITANIUM DIOXIDE

Inactive Ingredients:
Water, Cyclopentasiloxane, Ethylhexyl Methoxycinnamate, Cetyl Ethylhexanoate, Cyclomethicone, Dipropylene Glycol, 4-Methylbenzylidene Camphor, PEG-9 Polydimethylsiloxyethyl Dimethicone, Cetyl PEG/PPG-10/1 Dimethicone, Sorbitan Sesquioleate, Disteardimonium Hectorite, Benzophenone-3, Methylene Bis-Benzotriazolyl Tetramethylbutylphenol,
Glyceryl Behenate/Eicosadioate, Sodium Chloride, PEG-10 Dimethicone, Phenoxyethanol, Dimethicone Crosspolymer, Stearic Acid, Aluminum Hydroxide, Fragrance,
Butylparaben, Tocopheryl Acetate, Oryza Sativa (Rice) Bran Oil, Cellulose Gum, Ethylparaben, Methylparaben, Allantoin, Oryza Sativa (Rice) Bran Extract

Directions:
When you use or do leisure, apply reasonable amount on your body exposed to UV including face, neck, arms, and legs at your finishing step of basic makeup.
Take more frequent reapplication for longtime outdoor activities.
Notice for use:
1. Discontinue if the following symptom appears and consult with dermatologist for the continuos problem of use.
1) Discontinue use if redness, rash, irritation or tingling appears.
2) Discontinue if the above symptom appears by a direct sunlight on the applied part.
2. Avoid the part for a cut, eczema or dermatitis.
3. Please note for keeping and handling.
1) To keep the freshness, please close the lid after the use.
2) Keep this and all drugs out of reach of children.
3) Do not store this product in a place of high or low temperature. Do not expose it to the direct sunlight.
4) Be careful, it may be slipper when contact with the product.
5) Be careful not to make contacts with clothes.
6) Be careful not to give a shock since the container may be broken and get injured.
7) UV cutoff rating and SPF rating A of this product was measured in accordance with UV cutoff rating effect and methods examined by Korea Food and Drug Administration.